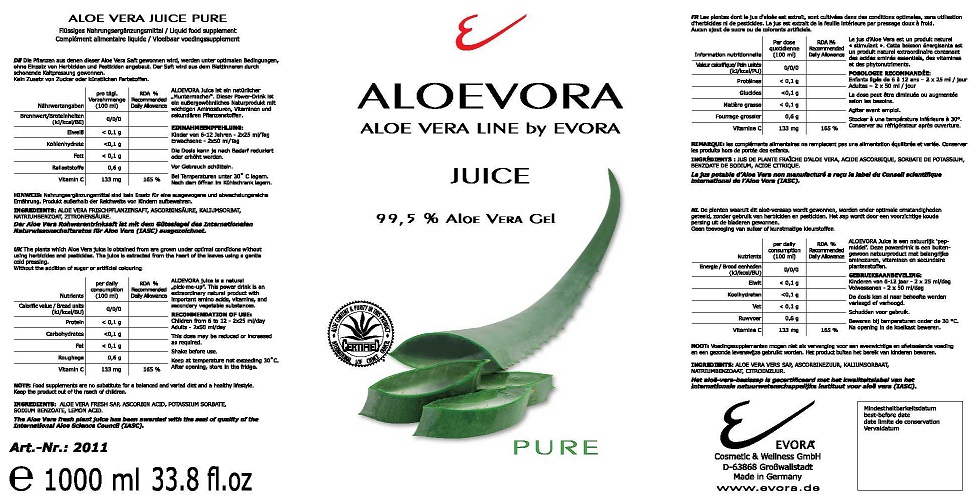 DRUG LABEL: ALOEVORA JUICE
NDC: 70822-102 | Form: SOLUTION
Manufacturer: EVORA Cosmetic and Wellness GmbH
Category: other | Type: Dietary Supplement
Date: 20190628

ACTIVE INGREDIENTS: ALOE VERA LEAF 99.5 g/100 mL
INACTIVE INGREDIENTS: ASCORBIC ACID; POTASSIUM SORBATE; SODIUM BENZOATE; LEMON

STATEMENT OF IDENTITY

ALOEVORA

ALOE VERA LINE BY EVORA

JUICE

99.5% ALOE VERA GEL